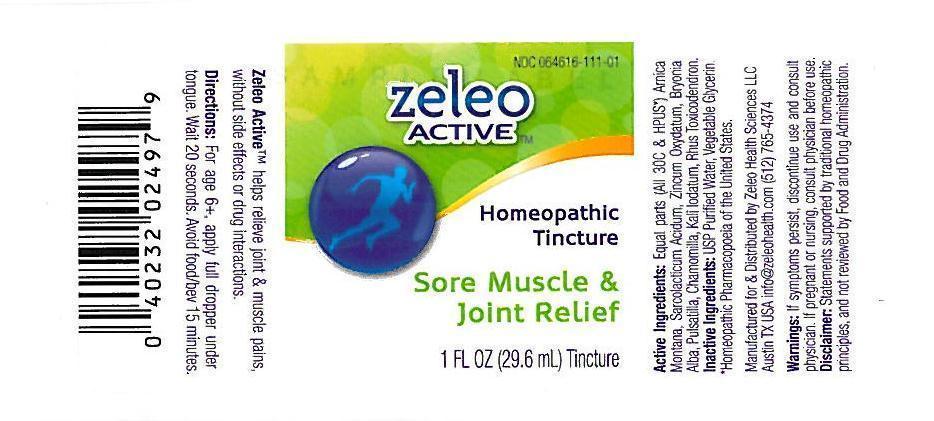 DRUG LABEL: Sore Muscle and Joint Relief
NDC: 64616-111 | Form: LIQUID
Manufacturer: Vitaltiy Works, Inc.
Category: homeopathic | Type: HUMAN OTC DRUG LABEL
Date: 20251217

ACTIVE INGREDIENTS: ARNICA MONTANA 30 [hp_C]/1 mL; BRYONIA ALBA ROOT 30 [hp_C]/1 mL; MATRICARIA RECUTITA 30 [hp_C]/1 mL; POTASSIUM IODIDE 30 [hp_C]/1 mL; PULSATILLA VULGARIS 30 [hp_C]/1 mL; TOXICODENDRON PUBESCENS LEAF 30 [hp_C]/1 mL; LACTIC ACID, L- 30 [hp_C]/1 mL; ZINC OXIDE 30 [hp_C]/1 mL
INACTIVE INGREDIENTS: GLYCERIN; WATER

Zeleo Active

Sore Muscle & Joint Relief

Arnica montana 30C Pulsatilla 30C

Bryona alba 30C Rhus toxicodendron 30C

Chamomilla 30C Sarcdolacticum acidum 30C

Kali iodatum 30C Zincum oxydatum 30C

Sore Muscle & Joint Relief

USP Vegetable Glycerin, USP Purified Water

Sore Muscle & Joint Relief

If symtoms persist, discontinue use and consult a physician. If pregnant or nursing, consult physician before use.

Sore Muscle & Joint Relief

Keep out of reach of children

Sore Muscle & Joint Relief

For temporary relief of joint and muscle pains.

Sore Muscle & Joint Relief

For age 6+, apply full dropper under tongue. Wait 20 seconds. Avoid food or beverages for 15 minutes.

Sore Muscle & Joint Relief

Aids in relieving of pain from muscles and joints.